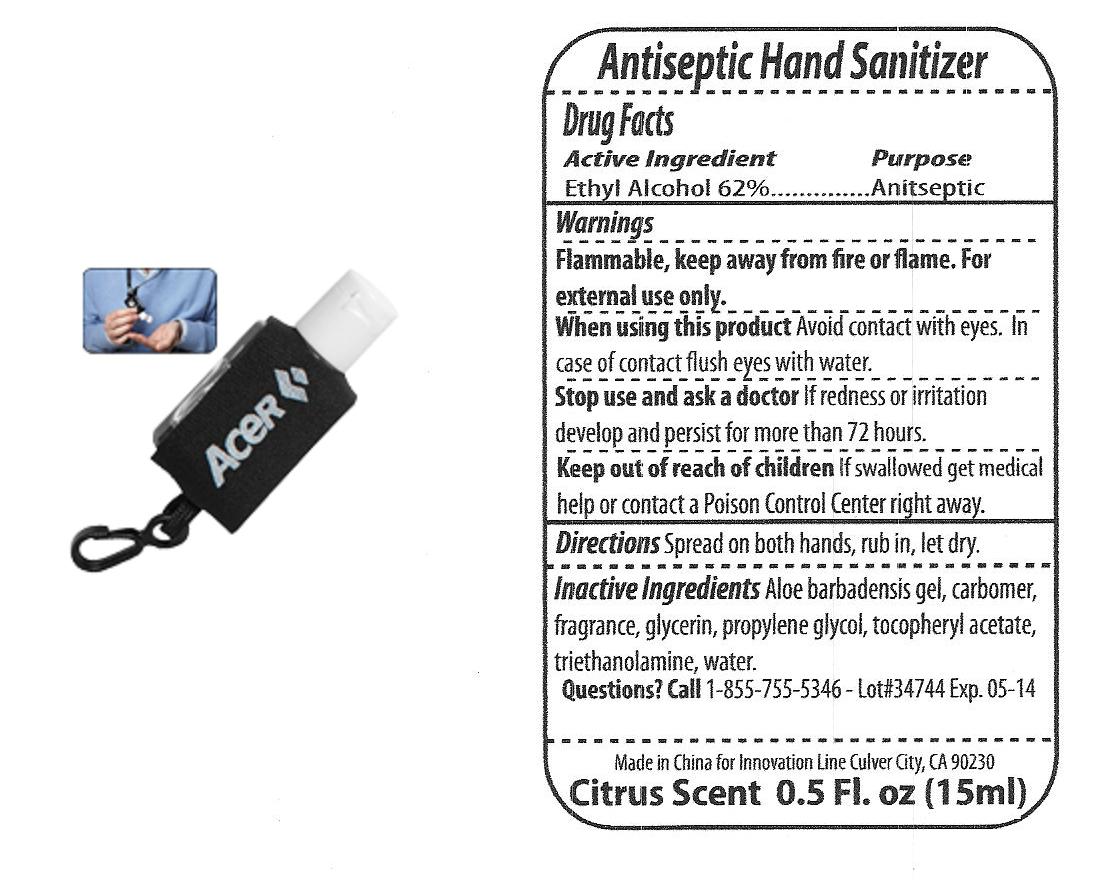 DRUG LABEL: Hand Sanitizer w/Carabiner
NDC: 76138-104 | Form: GEL
Manufacturer: INNOVATION SPECIALTIES
Category: otc | Type: HUMAN OTC DRUG LABEL
Date: 20121018

ACTIVE INGREDIENTS: ALCOHOL 62 mL/100 mL
INACTIVE INGREDIENTS: ALOE VERA LEAF; CARBOMER HOMOPOLYMER TYPE A; GLYCERIN; PROPYLENE GLYCOL; .ALPHA.-TOCOPHEROL ACETATE; TROLAMINE; WATER

Drug Facts

Active Ingredient

Ethyl Alcohol 62%

Purpose

Antiseptic

Keep out of reach of children If swallowed get medical help or contact a Poison Control Center right away.

Directions

Spread on both hands, rub in, let dry.

Warnings

Flammable, keep away from fire or flame, For external use only.

DOSAGE AND ADMINISTRATION

Spread on both hands, rub in, let dry.

Inactive Ingredients

Aloe Barbadensis Gel, Carbomer, Fragrance, Glycerin, Propylen Glycol, Tocopheryl Acetate, Triethanolamine, Water.

Questions ?

Call 1-855-755-5346